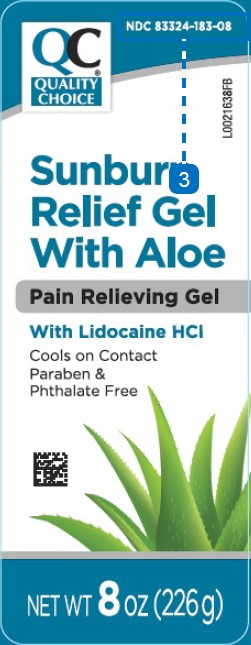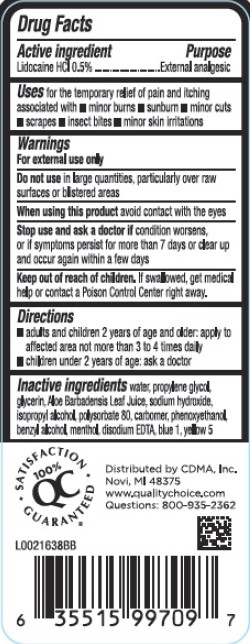 DRUG LABEL: Pain Relieving Gel
NDC: 83324-183 | Form: GEL
Manufacturer: Chain Drug Marketing Association
Category: otc | Type: HUMAN OTC DRUG LABEL
Date: 20260227

ACTIVE INGREDIENTS: LIDOCAINE HYDROCHLORIDE 5 mg/1 g
INACTIVE INGREDIENTS: WATER; PROPYLENE GLYCOL; GLYCERIN; ALOE VERA LEAF; SODIUM HYDROXIDE; ISOPROPYL ALCOHOL; POLYSORBATE 80; CARBOMER HOMOPOLYMER, UNSPECIFIED TYPE; PHENOXYETHANOL; BENZYL ALCOHOL; MENTHOL, UNSPECIFIED FORM; EDETATE DISODIUM; FD&C BLUE NO. 1; FD&C YELLOW NO. 5

Quality Choice 005.002/005AC-AD
Sunburn Relief Gel

Active ingredient

Lidocaine HCl 0.5%

Purpose

External analgesic

Uses

for the temporary relief of pain and itching associated with

- minor burns
- sunburn
- minor cuts
- scrapes
- insect bites
- minor skin irritations

Warnings

For external use only

Do not use

in large quantities, particularly over raw surfaces or blistered areas

When using this product

avoid contact with the eyes

Stop use and ask a doctor if

condition worsens, or if symptoms persist for more than 7 days or clear up and occur again within a few days

Keep out of reach of children.

If swallowed, get medical help or contact a Poison Control Center right away.

Directions

- adults and children 2 years of age and older: apply to affected area not more than 3 to 4 times daily
- children under 2 years of age: ask a doctor

Inactive ingredients

water, propylene glycol, glycerin, Aloe barbadensis leaf juice, sodium hydroxide, isopropyl alcohol, polysorbate 80, carbomer, phenoxyethanol, benzyl alcohol, menthol, disodium EDTA, blue 1, yellow 5

Adverse reaction

QC 100% SATISFACTION GUARANTEED

Distributed by CDMA, Inc.

Novi, MI 48375

www.qualitychoice.com

Questions: 800-935-2362

Principal panel display

NDC 83324-183-08

QC Quality Choice®

Sunburn

Relief Gel

With Aloe

Pain Relieveing Gel

With Lidocaince HCI

Cools on Contact

Paraben & Phthalate Free

NET WT 8oz (226 g)